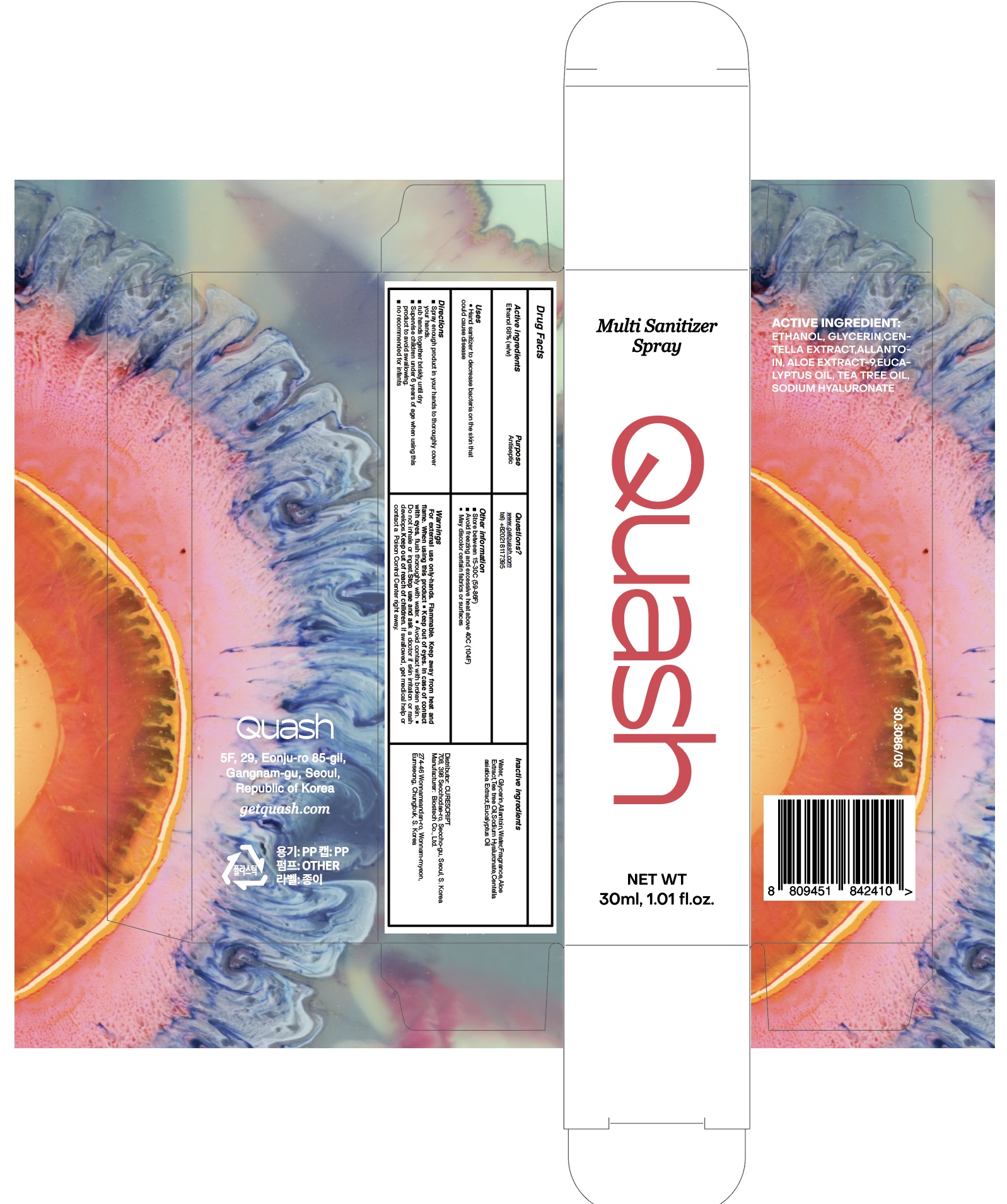 DRUG LABEL: QUASH MULTI SANITIZER
NDC: 72265-103 | Form: SPRAY
Manufacturer: CURESCRIPT
Category: otc | Type: HUMAN OTC DRUG LABEL
Date: 20210209

ACTIVE INGREDIENTS: ALCOHOL 20.4 g/30 mL
INACTIVE INGREDIENTS: Water; Glycerin; Allantoin; Aloe; TEA TREE OIL; HYALURONATE SODIUM; CENTELLA ASIATICA WHOLE; Eucalyptus Oil

ACTIVE INGREDIENT

Ethanol 68% (w/w)

INACTIVE INGREDIENTS

Water, Glycerin,Allantoin,Water,Fragrance,Aloe Extract, TEA TREE OIL,Sodium Hyaluronate,Centella asiatica Extract,Eucalyptus Oil

PURPOSE

Antiseptic

WARNINGS

For external use only-hands

Flammable. Keep away from heat and flame.

When using this product ■ Keep out of eyes. In case of contact with eyes, flush thoroughly with water. ■ Avoid contact with broken skin. ■ Do not inhale or ingest.

Stop use and ask a doctor if skin irritation or rash develops.

Keep out of reach of children. If swallowed, get medical help or contact a Poison Control Center right away.

KEEP OUT OF REACH OF CHILDREN

If swallowed, get medical help or contact a Poison Control Center right away.

Uses

■ Hand sanitizer to decrease bacteria on the skin that could cause disease

Directions

■ Spray enough product in your hands to thoroughly cover your hands.
■ rub hands together briskly until dry
■ Supervise children under 6 years of age when using this product to avoid swallowing.
■ no recommended for infants

Other Information

■ Store between 15-30C (59-86F)
■ Avoid freezing and excessive heat above 40C (104F)
■ May discolor certain fabrics or surfaces

QUESTIONS

www.getquash.com
tel) +820218117395